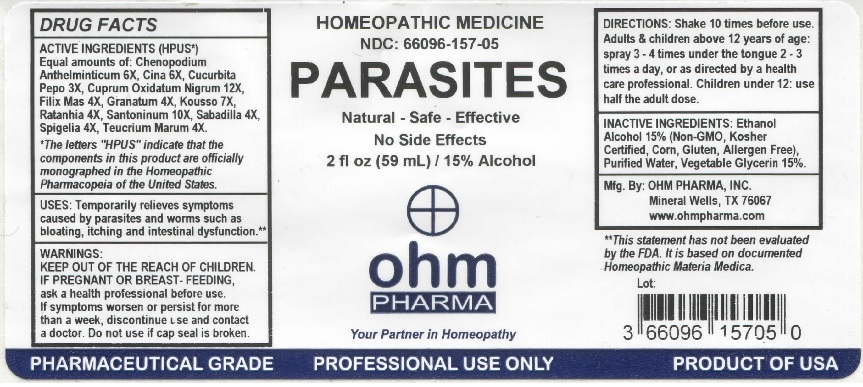 DRUG LABEL: OHM Parasites
NDC: 66096-157 | Form: LIQUID
Manufacturer: OHM PHARMA INC.
Category: homeopathic | Type: HUMAN PRESCRIPTION DRUG LABEL
Date: 20211229

ACTIVE INGREDIENTS: DYSPHANIA AMBROSIOIDES 6 [hp_X]/59 mL; ARTEMISIA CINA PRE-FLOWERING TOP 6 [hp_X]/59 mL; PUMPKIN SEED 3 [hp_X]/59 mL; CUPRIC OXIDE 12 [hp_X]/59 mL; DRYOPTERIS FILIX-MAS ROOT 4 [hp_X]/59 mL; PUNICA GRANATUM ROOT BARK 4 [hp_X]/59 mL; HAGENIA ABYSSINICA FLOWER 7 [hp_X]/59 mL; KRAMERIA LAPPACEA ROOT 4 [hp_X]/59 mL; SANTONIN 10 [hp_X]/59 mL; SCHOENOCAULON OFFICINALE SEED 4 [hp_X]/59 mL; SPIGELIA MARILANDICA ROOT 4 [hp_X]/59 mL; TEUCRIUM MARUM 4 [hp_X]/59 mL
INACTIVE INGREDIENTS: ALCOHOL; WATER; GLYCERIN

OHM Parasites

ACTIVE INGREDIENT

ACTIVE INGREDIENTS (HPUS*) Equal amounts of: Chenopodium Anthelminticum 6X, Cina 6X, Cucurbita Pepo 3X, Cuprum Oxydatum Nigrum 12X, Filix Mas 4X, Granatum 4X, Kousso 7X, Ratanhia 4X, Santoninum 10X, Sabadilla 4X, Spigelia 4X, Teucrium Marum 4X.

*The letters "HPUS" indicate that the components in this product are officially monographed in the Homeopathic Pharmacopeia of the United States.

INDICATIONS AND USAGE

USES: Temporarily relieves symptoms caused by parasites and worms such as bloating, itching and intestinal dysfunction.**

** This statement has not been evaluated by the FDA. It is based on documented Homeopathic Materia Medica.

WARNINGS

WARNINGS: IF PREGNANT OR BREAST-FEEDING, ask a health professional before use. If symptoms worsen or persist for more than a week, discontinue use and contact a doctor.

- KEEP OUT OF REACH OF CHILDREN.

DOSAGE AND ADMINISTRATION

DIRECTIONS: Shake 10 times before use. Adults & children above 12 years of age: spray 3-4 times under the tongue 2-3 times a day, or as directed by a health care professional. Children under 12: use half the adult dose.

Do not use if cap seal is broken.

INACTIVE INGREDIENT

INACTIVE INGREDIENTS: Ethanol Alcohol 15% (Non-GMO, Kosher Certified, Corn, Gluten, Allergen Free), Purified Water, Vegetable Glycerin 15%.

QUESTIONS

Mfg. By: OHM PHARMA, INC. Mineral Wells, TX 76067

www.ohmpharma.com

PACKAGE LABEL

HOMEOPATHIC MEDICINE

NDC: 66096-157-05

PARASITES

Natural - Safe - Effective

No Side Effects

2 fl oz (59 mL) / 15% Alcohol

PRODUCT OF USA

PURPOSE

Relieves symptoms caused by parasites and worms.